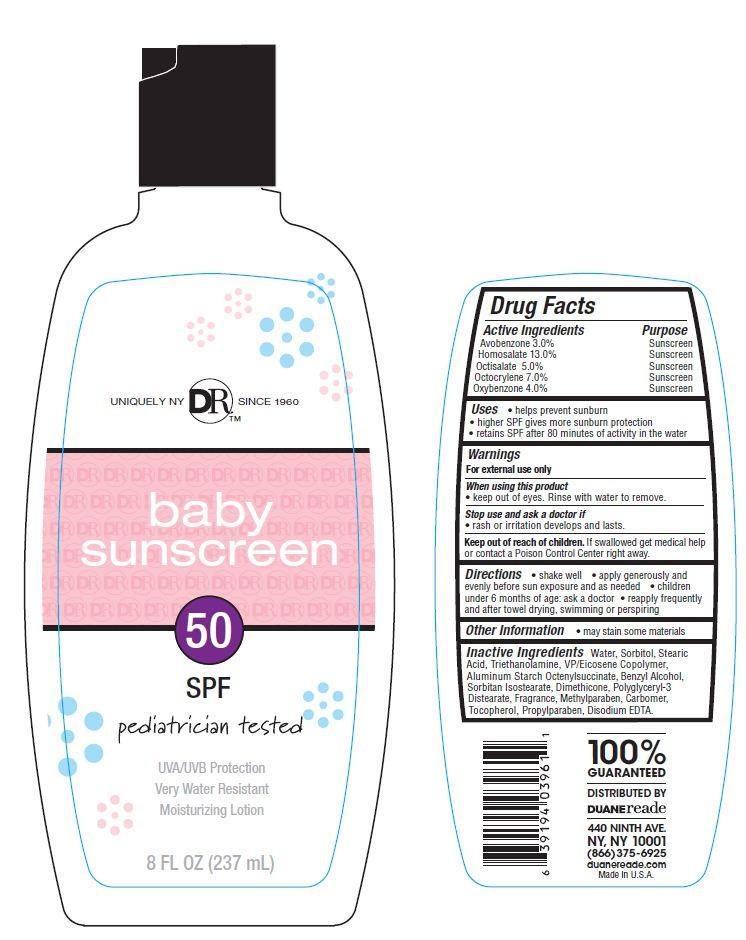 DRUG LABEL: Duane Reade Baby SunscreenSPF 50
          
NDC: 67732-401 | Form: LOTION
Manufacturer: DUANE READE INC.
Category: otc | Type: HUMAN OTC DRUG LABEL
Date: 20121113

ACTIVE INGREDIENTS: AVOBENZONE 3 g/100 g; HOMOSALATE 13 g/100 g; OCTISALATE 5 g/100 g; OCTOCRYLENE 7 g/100 g; OXYBENZONE 4 g/100 g
INACTIVE INGREDIENTS: WATER; SORBITOL; STEARIC ACID; TROLAMINE; ALUMINUM STARCH OCTENYLSUCCINATE; BENZYL ALCOHOL; SORBITAN ISOSTEARATE; DIMETHICONE; POLYGLYCERYL-3 DIISOSTEARATE; METHYLPARABEN; PROPYLPARABEN; TOCOPHEROL; EDETATE DISODIUM

Drug Facts

Active Ingredients

Avobenzone 3.0 %

Homosalate 13.0%

Octisalate 5.0%

Octocrylene 7.0%

Oxybenzone 4.0%

Purpose

Sunscreen

Uses

- helps prevent sunburn
- higher SPF gives more sunburn protection
- retains SPF after 80 minutes of activity in the water

Warnings

For external use only

When using this product

- keep out of eyes. Rinse with water to remove.

Stop use and ask a doctor if

- rash or irritation develops and lasts

Keep out of reach of children.

If swallowed get medical help or contact a Poison Control Center right away.

Other Information

- may stain some materials

Directions

- shake well
- apply generously before sun exposure and as needed
- Children under 6 months of age:ask a doctor
- reapplying frequently after towel drying, swimming or perspiring.

Inactive Ingredients

Water, Stearic Acid, Sorbitol,Triethanolamine,VP/Eicosene Copolymer, Aluminium Starch Octenylsuccinate, Benzyl Alcohol, Sorbitan Isostearate, Dimethicone, Polyglyceryl-3 Diastearate, Fragrance, Methylparaben, Carbomer, Tocopherol, Propylparaben, Disodium EDTA

Principal Display Panel

UNIQUELY NY DRTM SINCE 1960

baby

SUNSCREEN
50
SPF

pediatrician tested

UVA/UVB Protection
Very Water Resistant

Moisturizing Lotion

8 FL OZ (237 mL)